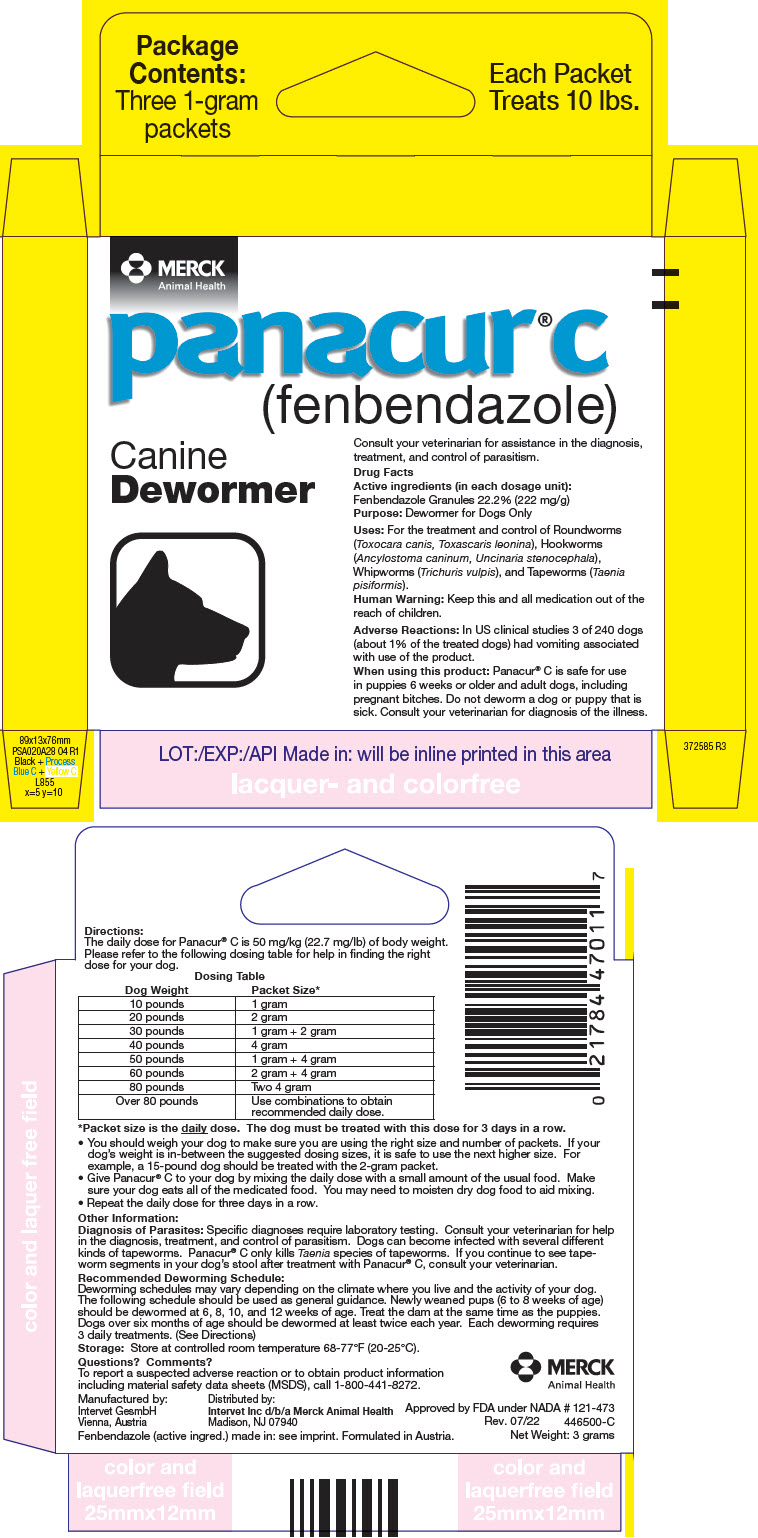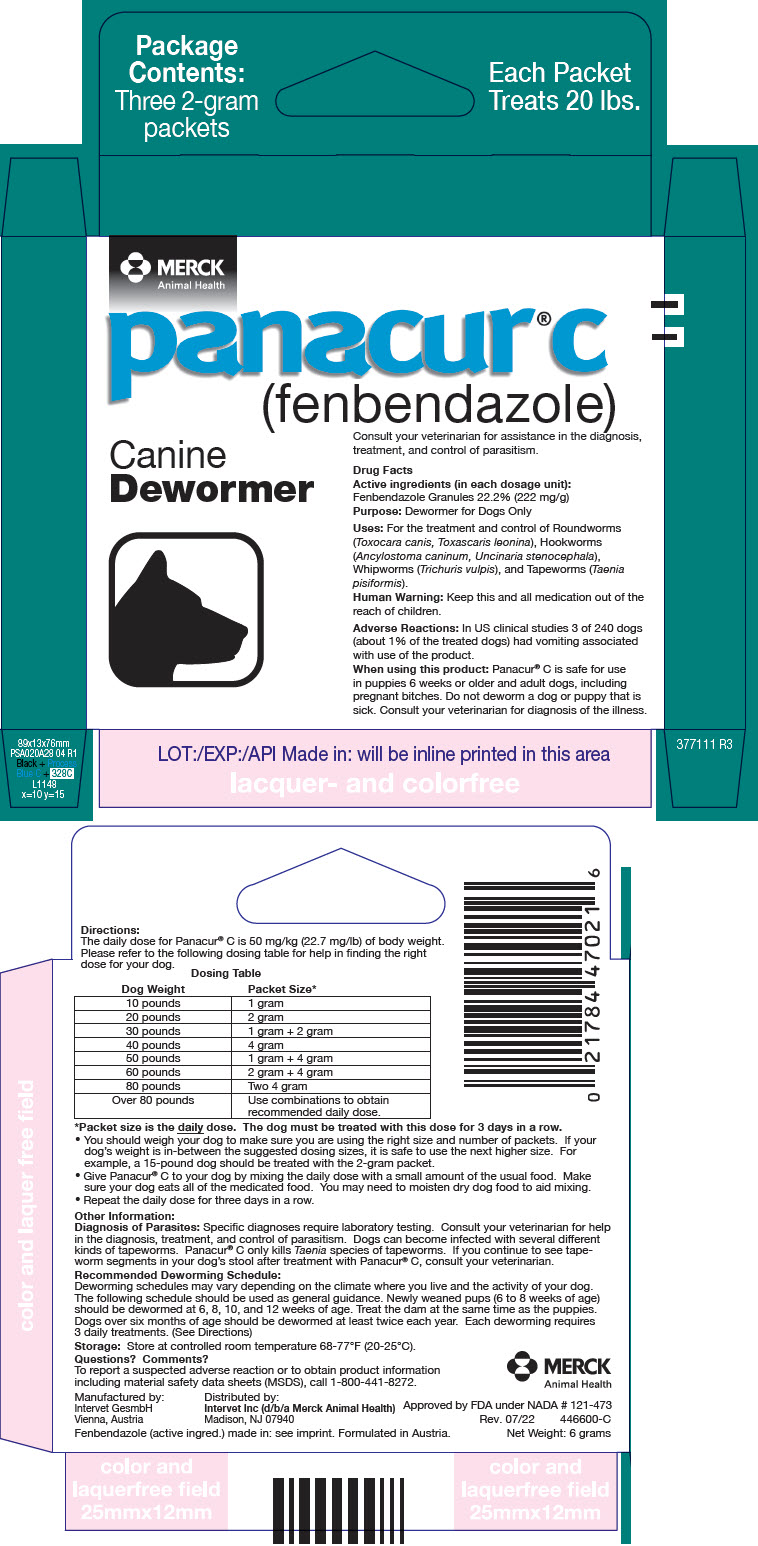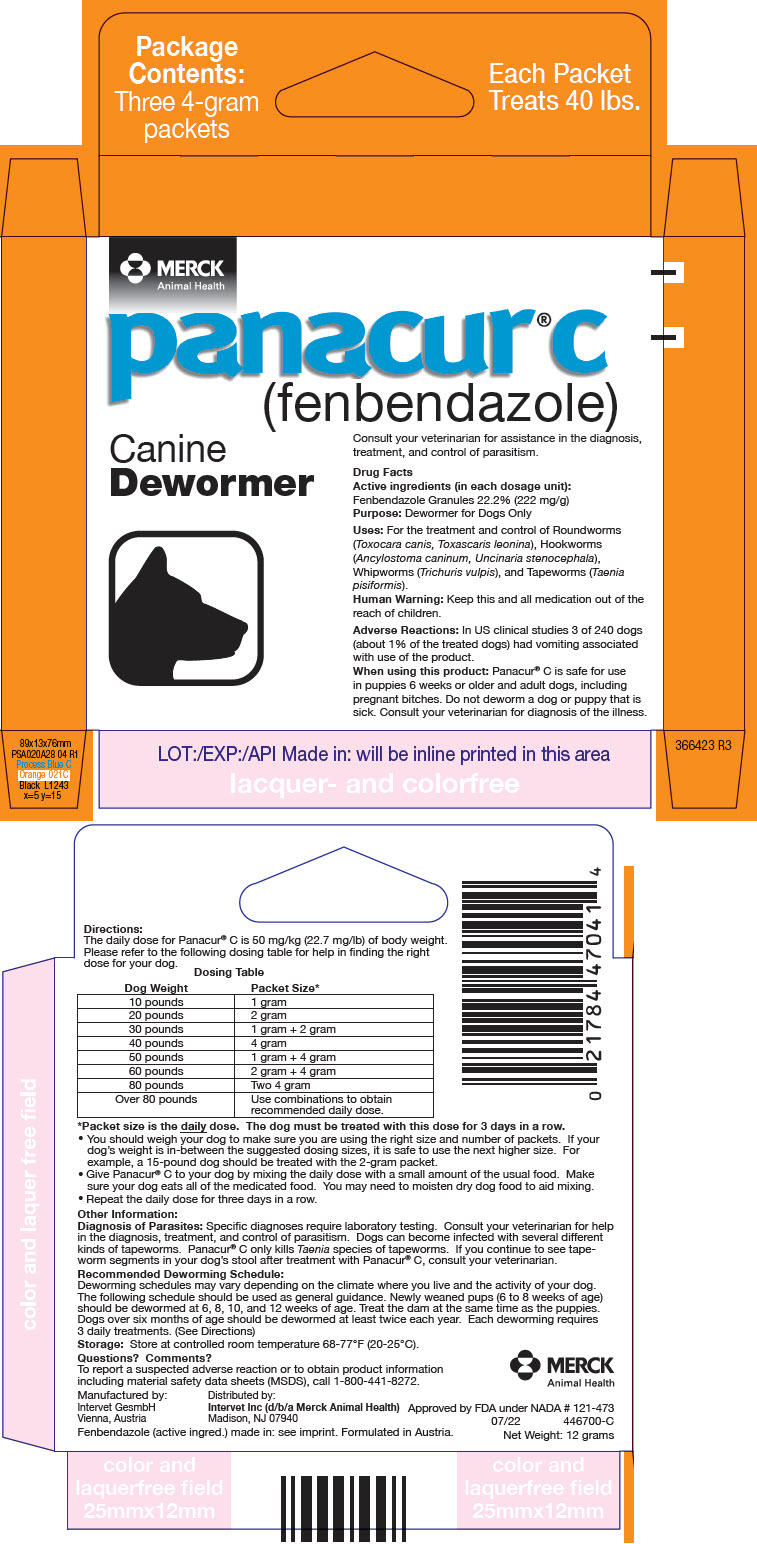 DRUG LABEL: Panacur C Canine
NDC: 57926-480 | Form: GRANULE
Manufacturer: Merck Sharp & Dohme Corp.
Category: animal | Type: OTC ANIMAL DRUG LABEL
Date: 20241114

ACTIVE INGREDIENTS: FENBENDAZOLE 222 mg/1 g

panacur® c
(fenbendazole)

Drug Facts

Active ingredients (in each dosage unit):

Fenbendazole Granules 22.2% (222 mg/g)

Purpose: Dewormer for Dogs Only

INDICATIONS AND USAGE

Uses: For the treatment and control of Roundworms (Toxocara canis, Toxascaris leonina), Hookworms (Ancylostoma caninum, Uncinaria stenocephala), Whipworms (Trichuris vulpis), and Tapeworms (Taenia pisiformis).

WARNINGS

Human Warning: Keep this and all medication out of the reach of children.

ADVERSE REACTIONS

Adverse Reactions: In US clinical studies 3 of 240 dogs (about 1% of the treated dogs) had vomiting associated with use of the product.

When using this product: Panacur® C is safe for use in puppies 6 weeks or older and adult dogs, including pregnant bitches. Do not deworm a dog or puppy that is sick. Consult your veterinarian for diagnosis of the illness.

Directions:

The daily dose for Panacur® C is 50 mg/kg (22.7 mg/lb) of body weight. Please refer to the following dosing table for help in finding the right dose for your dog.

Dosing Table
Dog Weight | Packet Size [Packet size is the daily dose. The dog must be treated with this dose for 3 days in a row.]
10 pounds | 1 gram
20 pounds | 2 gram
30 pounds | 1 gram + 2 gram
40 pounds | 4 gram
50 pounds | 1 gram + 4 gram
60 pounds | 2 gram + 4 gram
80 pounds | Two 4 gram
Over 80 pounds | Use combinations to obtain recommended daily dose.

- You should weigh your dog to make sure you are using the right size and number of packets. If your dog's weight is in-between the suggested dosing sizes, it is safe to use the next higher size. For example, a 15-pound dog should be treated with the 2-gram packet.
- Give Panacur® C to your dog by mixing the daily dose with a small amount of the usual food. Make sure your dog eats all of the medicated food. You may need to moisten dry dog food to aid mixing.
- Repeat the daily dose for three days in a row.

Other Information:

Diagnosis of Parasites: Specific diagnoses require laboratory testing. Consult your veterinarian for help in the diagnosis, treatment, and control of parasitism. Dogs can become infected with several different kinds of tapeworms. Panacur® C only kills Taenia species of tapeworms. If you continue to see tapeworm segments in your dog's stool after treatment with Panacur® C, consult your veterinarian.

Recommended Deworming Schedule:

Deworming schedules may vary depending on the climate where you live and the activity of your dog. The following schedule should be used as general guidance. Newly weaned pups (6 to 8 weeks of age) should be dewormed at 6, 8, 10, and 12 weeks of age. Treat the dam at the same time as the puppies. Dogs over six months of age should be dewormed at least twice each year. Each deworming requires 3 daily treatments. (See Directions)

STORAGE AND HANDLING

Storage: Store at controlled room temperature 68-77°F (20-25°C).

Questions? Comments?

To report a suspected adverse reaction or to obtain product information including material safety data sheets (MSDS), call 1-800-441-8272.

Manufactured by:
Intervet GesmbH
Vienna, Austria

Distributed by:
Intervet Inc d/b/a Merck Animal Health
Madison, NJ 07940

Approved by FDA under NADA # 121-473
Rev. 07/22
446500-C
Net Weight: 3 grams

Fenbendazole (active ingred.) made in: see imprint. Formulated in Austria.

PRINCIPAL DISPLAY PANEL - 1 g Packet Carton

MERCK
Animal Health

panacur® c
(fenbendazole)

Canine
Dewormer

Consult your veterinarian for assistance in the diagnosis,
treatment, and control of parasitism.

PRINCIPAL DISPLAY PANEL - 2 g Packet Carton

MERCK
Animal Health

panacur® c
(fenbendazole)

Canine
Dewormer

Consult your veterinarian for assistance in the diagnosis,
treatment, and control of parasitism.

PRINCIPAL DISPLAY PANEL - 4 g Packet Carton

MERCK
Animal Health

panacur® c
(fenbendazole)

Canine
Dewormer

Consult your veterinarian for assistance in the diagnosis,
treatment, and control of parasitism.